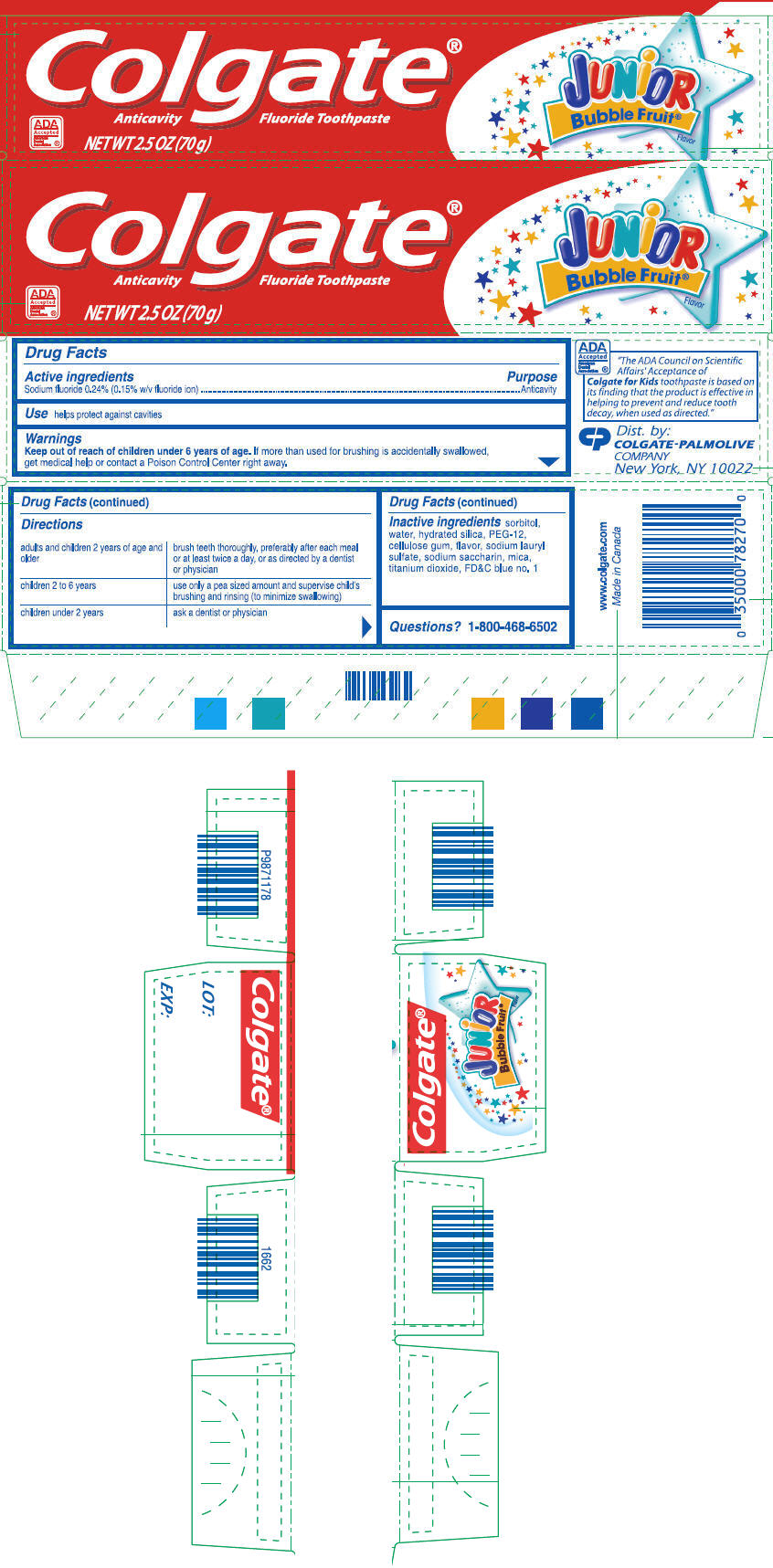 DRUG LABEL: Colgate 
NDC: 51442-327 | Form: GEL, DENTIFRICE
Manufacturer: Colgate-Palmolive Canada
Category: otc | Type: HUMAN OTC DRUG LABEL
Date: 20110727

ACTIVE INGREDIENTS: Sodium Fluoride 2.4 mg/1 g
INACTIVE INGREDIENTS: sorbitol; water; hydrated silica; Polyethylene Glycol 600; Carboxymethylcellulose Sodium; sodium lauryl sulfate; Saccharin Sodium; mica; titanium dioxide; FD&C Blue no. 1

Colgate®
JUNiOR
Bubble Fruit®

Drug Facts

Active ingredients

Sodium fluoride 0.24% (0.15% w/v fluoride ion)

Purpose

Anticavity

Use

helps protect against cavities

Warnings

Keep out of reach of children under 6 years of age. If more than used for brushing is accidentally swallowed, get medical help or contact a Poison Control Center right away.

Directions

adults and children 2 years of age and older | brush teeth thoroughly, preferably after each meal or at least twice a day, or as directed by a dentist or physician
children 2 to 6 years | use only a pea sized amount and supervise child's brushing and rinsing (to minimize swallowing)
children under 2 years | ask a dentist or physician

Inactive ingredients

sorbitol, water, hydrated silica, PEG-12, cellulose gum, flavor, sodium lauryl sulfate, sodium saccharin, mica, titanium dioxide, FD&C blue no. 1

Questions?

1-800-468-6502

Dist. by:
COLGATE-PALMOLIVE
COMPANY
New York, NY 10022

PRINCIPAL DISPLAY PANEL - 70 g Carton

Colgate®
Anticavity Fluoride Toothpaste

ADA
Accepted
American
Dental
Association ®

NET WT 2.5 OZ (70 g)

JUNiOR
Bubble Fruit®
Flavor